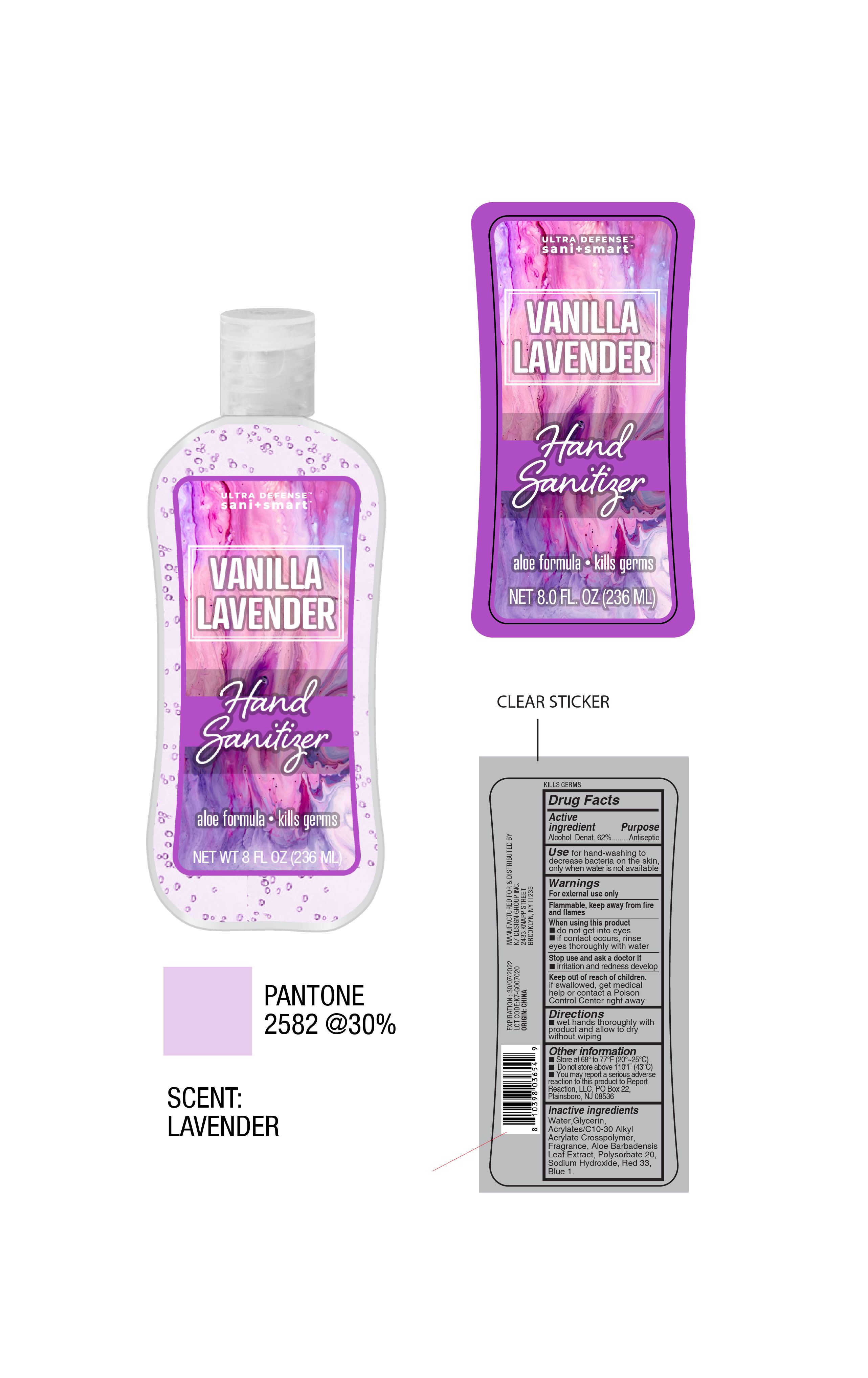 DRUG LABEL: Ultra Defense Sani Smart Vanilla Lavender Hand Sanitizer
NDC: 51522-055 | Form: GEL
Manufacturer: Gold Orient International Limited
Category: otc | Type: HUMAN OTC DRUG LABEL
Date: 20200806

ACTIVE INGREDIENTS: ALCOHOL 62 mL/100 mL
INACTIVE INGREDIENTS: WATER; GLYCERIN; POLYSORBATE 20; CARBOMER INTERPOLYMER TYPE A (ALLYL SUCROSE CROSSLINKED); ALOE VERA LEAF; D&C RED NO. 33; FD&C BLUE NO. 1; SODIUM HYDROXIDE

Ultra Defense Sani Smart Vanilla Lavender Hand Sanitizer

Active ingredient

Alcohol Denat. 62%

Purpose

Antiseptic

Use

Use for hand-washing to decrease bacteria on the skin, only when water it not available.

Warnings

For external use only. Flammable, keep away from fire and flames.

When using this product

Do not get into eyes.

If contact occurs, rinse eyes thoroughly with water.

Stop use and ask a doctor if

If irritation and redness develop.

Keep out of reach of children

If swallowed, get medical help or contact a Poison Control Center right away.

Directions

Wet hands thoroughly with product and allow to dry without wiping.

Other information

Store at 68 to 77F (20-25C)

Do not store above 110F (43C)

You may report a serious adverse reaction to this product to Report Reaction, LLC, PO Box 22, Plainsboro, NJ 08536

Inactive ingredients

Water,

Glycerin,

Acrylates/C10-30 Alkyl Acrylate Crosspolymer,

Fragrance,

Aloe Barbadensis Leaf Extract,

Polysorbate 20,

Sodium Hydroxide,

Red 33,

Blue 1